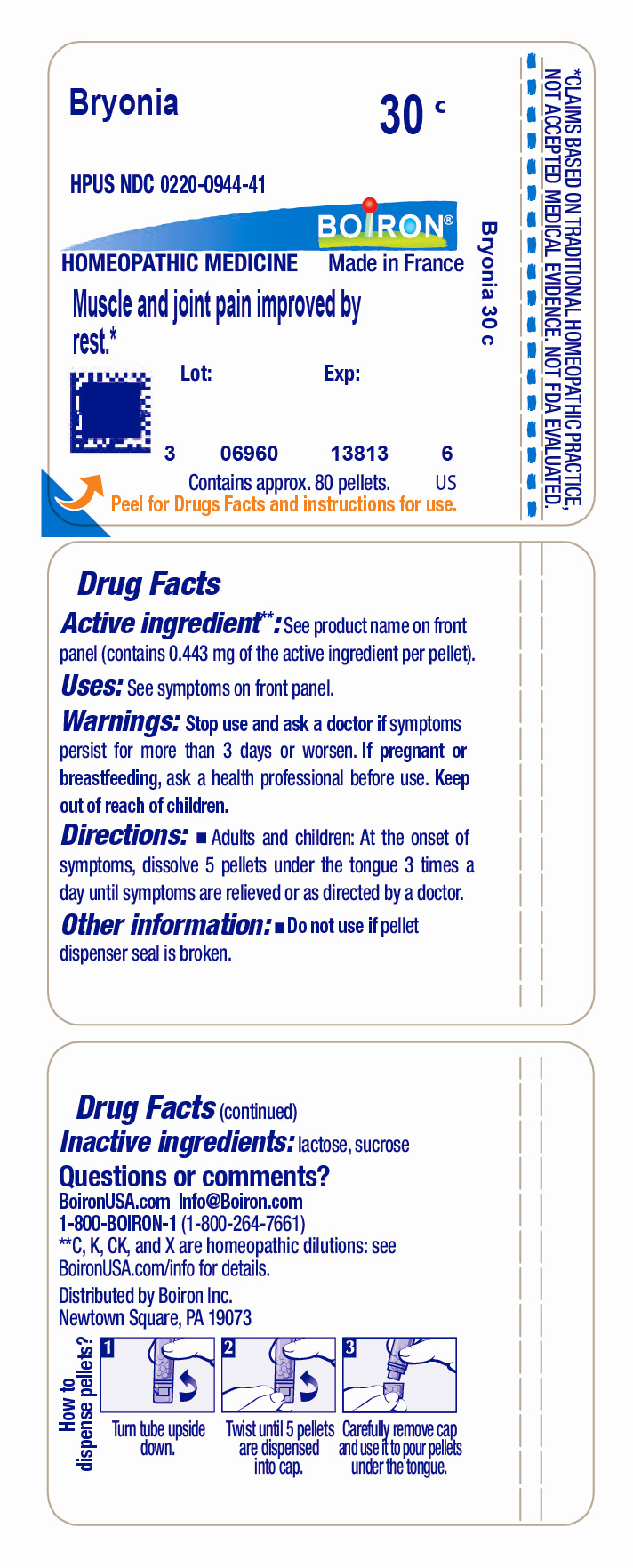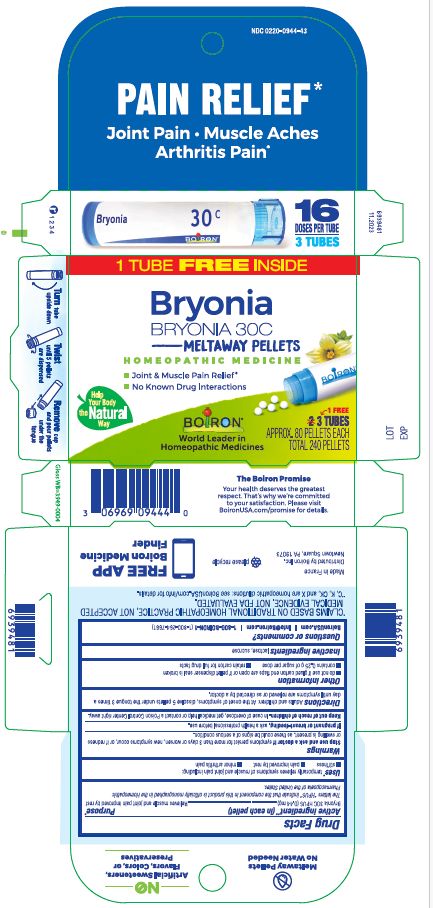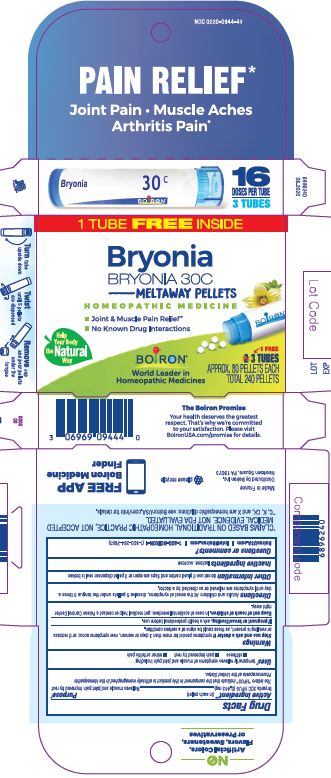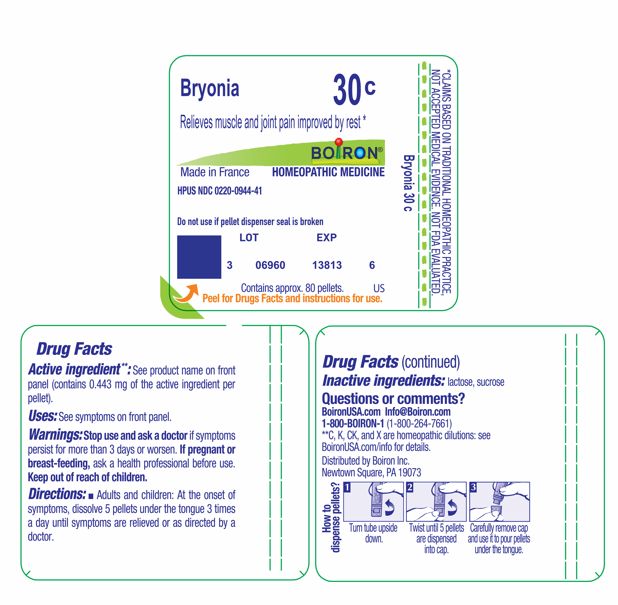 DRUG LABEL: Bryonia
NDC: 0220-0944 | Form: PELLET
Manufacturer: Boiron
Category: homeopathic | Type: HUMAN OTC DRUG LABEL
Date: 20260102

ACTIVE INGREDIENTS: BRYONIA ALBA ROOT 30 [hp_C]/30 [hp_C]
INACTIVE INGREDIENTS: SUCROSE; LACTOSE, UNSPECIFIED FORM

Bryonia 30C

Active ingredient** (in each pellet)

Bryonia 30C HPUS (0.44 mg)

The letters "HPUS" indicate that the component in this product are officially monographed in the Homeopathic Pharmacopoeia of the United States.

Purpose*

Relieves muscle and joint pain improved by rest

INDICATIONS AND USAGE

temporarily relieves symptoms of muscle and joint pain including:

- stiffness
- pain improved by rest
- minor arthritis pain

Stop use and ask a doctor if symptoms persist for more than 3 days or worsen, new symptoms occur, or if redness or swelling is present, as these could be signs of serious condition

PREGNANCY OR BREAST FEEDING

If pregnant or breast-feeding, ask a health professional before use.

Keep out of reach of children. In case of overdose, get medical help or contact a Poison Control Center right away.

DOSAGE AND ADMINISTRATION

Adults and children: At the onset of symptoms, dissolve 5 pellets under the tongue 3 times a day until symptoms are relieved or as directed by a doctor.

INACTIVE INGREDIENT

lactose, sucrose

QUESTIONS

BoironUSA.com Info@boiron.com

1-800-BOIRON-1 (1-800-264-7661)
Distributed by Boiron, Inc.

Newtown Square, PA 19073

Do not use if pellet dispenser seal is broken.
Do not use if glued carton end flaps are open or if pellet dispenser seal is broken.

1 Tube approx 80 pellets

3 Tubes approx 80 pellets 16 Doses per tube Total 240 pellets

How to dispense pellets? Turn tube upside down. Twist until 5 pellets are dispensed. Remove cap and pour pellets under the tongue.

Pain Relief*

Joint Pain Muscle Aches Arthritis Pain*

No known drug interactions

Joint & Muscle Pain Relief*

*CLAIMS BASED ON TRADITIONAL HOMEOPATHIC PRACTICE NOT ACCEPTED MEDICAL EVIDENCE. NOT FDA EVALUATED.
*C,K,CK, and X are homeopathic dilutions: see BoironUSA.com/info for details.